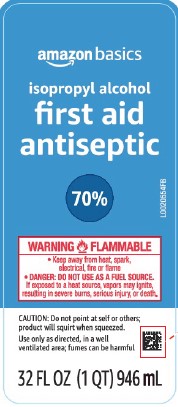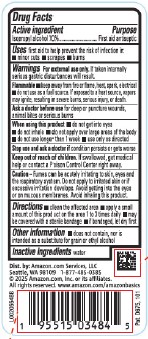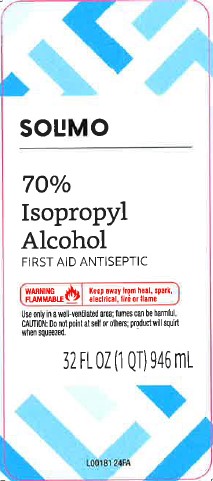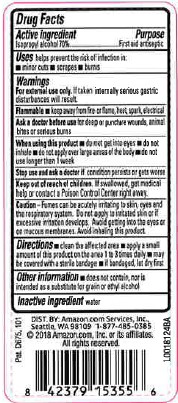 DRUG LABEL: 70% Isopropyl Alcohol
NDC: 72288-810 | Form: LIQUID
Manufacturer: Amazon.Com Services LLC
Category: otc | Type: HUMAN OTC DRUG LABEL
Date: 20251125

ACTIVE INGREDIENTS: ISOPROPYL ALCOHOL 70 mL/100 mL
INACTIVE INGREDIENTS: WATER

Basics_Solimo 810.003/810AA
Isopropyl Alcohol 70%

Active ingredient

Isopropyl alcohol 70%

Purpose

First Aid Antiseptic

Uses

First aid to help prevent the risk of infection in:

- minor cuts
- scrapes
- burns

Warnings

For external use only. If taken internally serious gastric disturbances will result.

Flammable.

- keep away from fire or flame, heat, spark, electrical
- do not use as a fuel source. If exposed to a heat source, vapors may ignite, resulting in severe burns, serious injury, or death.

Ask a doctor before use

for deep or puncture wounds, animal bites or serious burns

When using this product

- do not get into eyes
- do not inhale
- do not apply over large area of the body
- do not use longer than 1 week
- use only as directed

Stop use and ask a doctor if

condition persists or gets worse

Keep out of reach of children.

If swallowed, get medical hep or contact a Poison Control Center right away.

Caution

Fumes can be acutely irritating to skin, eyes and the respiratory system. Do not apply to irritated skin or if excessive irritation develops. Avoid getting into the eyes or on mucous membranes. Avoid inhaling this product.

Directions

- clean the affected area
- apply a small amount of this product on the affected area 1 to 3 times daily
- may be covered with a sterile bandage
- if bandaged, let dry first

Other information

- does not contain, nor is intended as a substitute for grain or ethyl alcohol

Inactive ingredient

water

ADVERSE REACTION

Dist. by: Amazon.com, Services, LLC

Seattle, WA 98109 1-877-485-0385

©2025 Amazon.com, Inc. or its afiliates.

All rights reserved. www.amazon.com/amazonbasics

Pat. D675,101

principal display panel

Solimo

70% Isopropyl Alcohol

First Aid Antiseptic

WARNING FLAMMABLE - Keep away from heat, spark, electrical, fire or flame

Use only in a well-ventilated area; fumes can be harmful

Caution: Do not point at self or others; product will squirt when squeezed.

32 FL OZ (1 QT) 946 mL

PRINCIPAL DISPLAY PANEL

amazon basics

Isopropyl Alcohol

First Aid Antiseptic

70%

WARNING FLAMMABLE

- Keep away from heat, spark, electrical, fire or flame
- DANGER: DO NOT USE AS A FUEL SOURCE. If exposed to a heat source, vapors may ignite, resulting in severe burns, serious injury, or death.

Caution: Do not point at self or others; product will squirt when squeezed.

Use only as directed, in a well-ventilated area; fumes can be harmful

32 FL OZ (1 QT) 946 mL